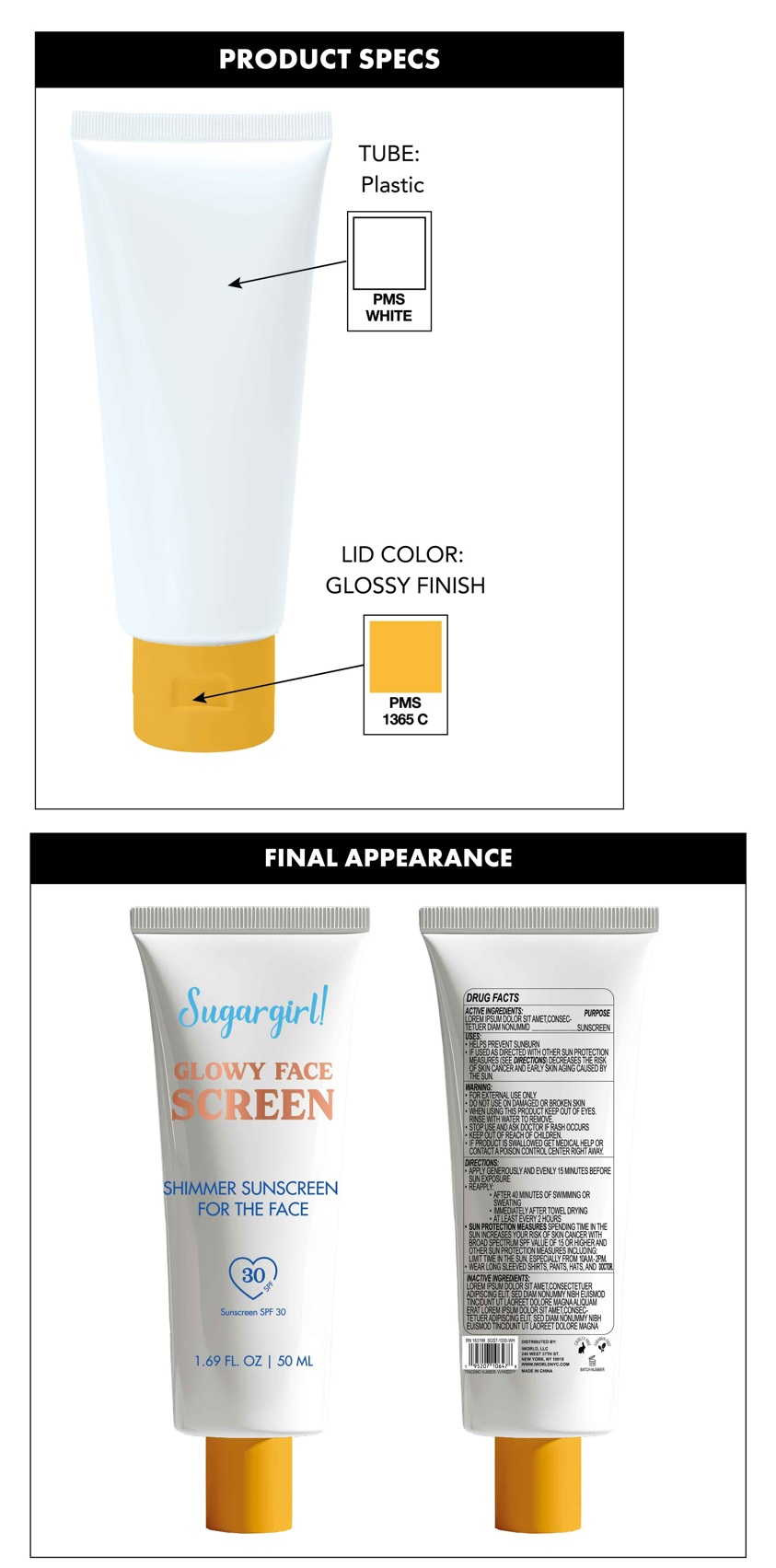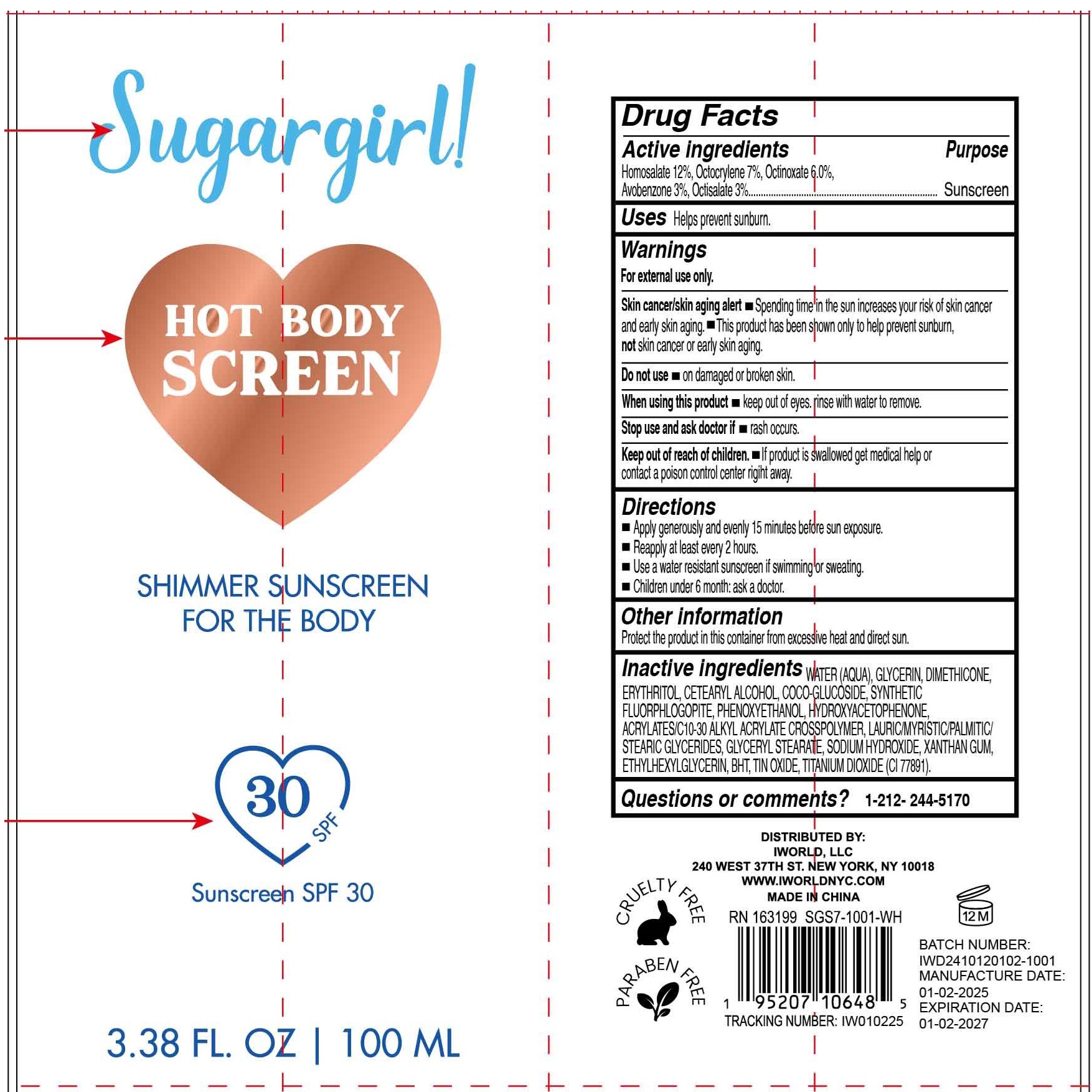 DRUG LABEL: Sugargirl Hot Body Screen Shimmer Sunscreen SPF 30
NDC: 85179-004 | Form: LOTION
Manufacturer: I World LLC
Category: otc | Type: HUMAN OTC DRUG LABEL
Date: 20250120

ACTIVE INGREDIENTS: HOMOSALATE 120 mg/1 mL; OCTOCRYLENE 70 mg/1 mL; OCTINOXATE 60 mg/1 mL; AVOBENZONE 30 mg/1 mL; OCTISALATE 30 mg/1 mL
INACTIVE INGREDIENTS: WATER; GLYCERIN; DIMETHICONE; ERYTHRITOL; CETEARYL ALCOHOL; COCO-GLUCOSIDE; PHENOXYETHANOL; HYDROXYACETOPHENONE; GLYCERYL MONOSTEARATE; SODIUM HYDROXIDE; XANTHAN GUM; ETHYLHEXYLGLYCERIN; BUTYLATED HYDROXYTOLUENE; STANNIC OXIDE; TITANIUM DIOXIDE

Sugargirl Hot Body Screen Shimmer Sunscreen SPF 30

Active ingredients

Homosalate 12%, Octocrylene 7%, Octinoxate 6%, Avobenzone 3%, Octisalate 3%

Purpose

Sunscreen

Uses

Helps prevent sunburn.

Warnings

For external use only.

Skin cancer/skin aging alert • Spending time in the sun increases your risk of skin cancer and early skin aging.

• This product has been shown only to help prevent sunburn, notskin cancer or early skin aging.

Do not use

- on damaged or broken skin.

When using this product

- Keep out of eyes. rinse with water to remove.

Stop use and ask doctor if

- rash occurs.

Keep out of reach of children.

- If product is swallowed get medical help or contact a Poison Control Center right away.

Directions

- Apply generously and evenly 15 minutes before sun exposure.
- Reapply at least every 2 hours.
- Use a water resistant sunscreen if swimming or sweating.
- Children under 6 month: ask a doctor.

Other information

Protect the product in this container from excessive heat and direct sun.

Inactive ingredients

WATER (AQUA), GLYCERIN, DIMETHICONE, ERYTHRITOL, CETEARYL ALCOHOL, COCO-GLUCOSIDE, SYNTHETIC FLUORPHLOGOPITE, PHENOXYETHANOL, HYDROXYACETOPHENONE, ACRYLATES/C10-30 ALKYL ACRYLATE CROSSPOLYMER, LAURIC/MYRISTIC/PALMITIC/ STEARIC GLYCERIDES, GLYCERYL STEARATE, SODIUM HYDROXIDE, XANTHAN GUM, ETHYLHEXYLGLYCERIN, BHT, TIN OXIDE, TITANIUM DIOXIDE (CI 77891).

Questions or comments?

1-212-244-5170